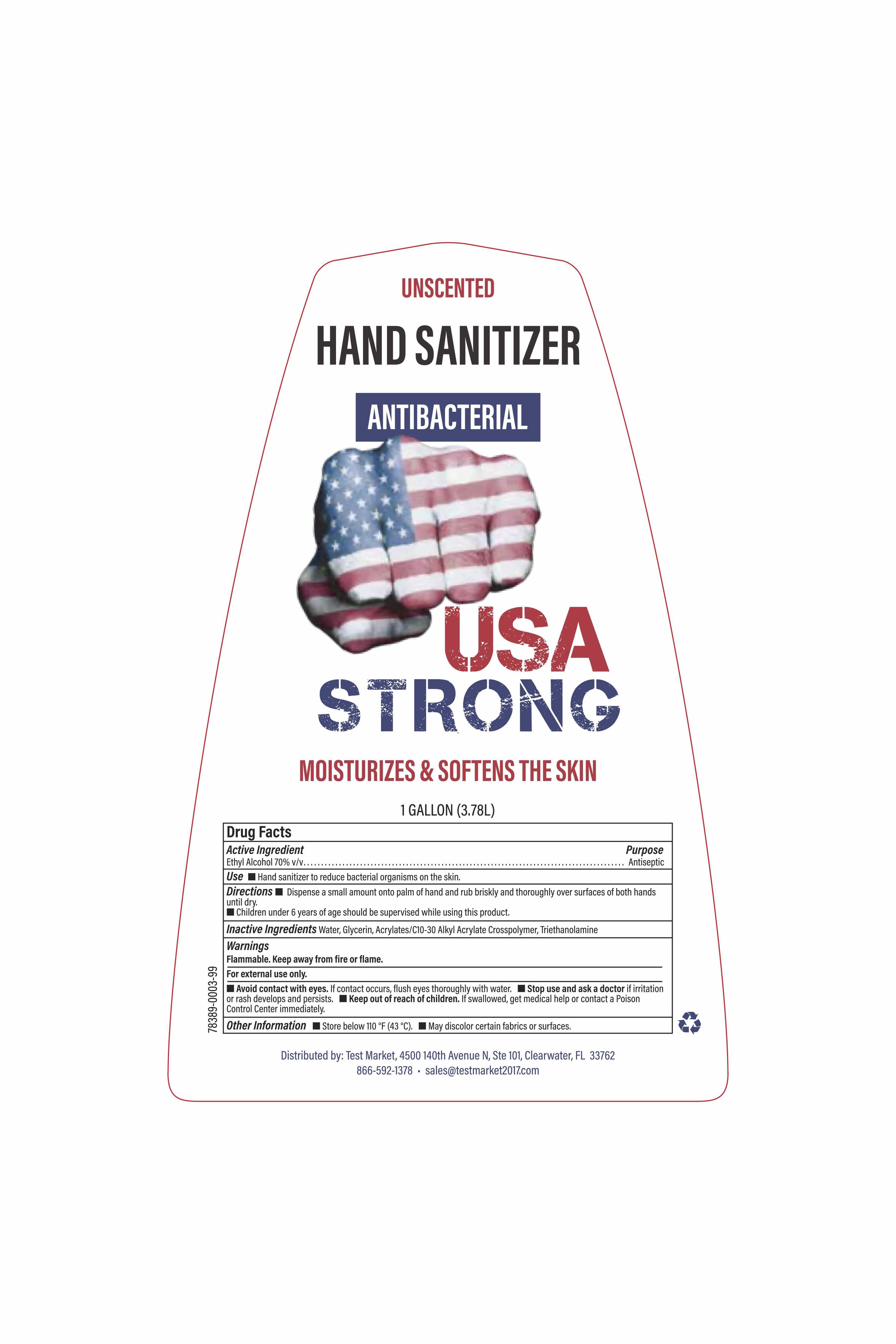 DRUG LABEL: Hand Sanitizer
NDC: 78389-003 | Form: GEL
Manufacturer: ABSOLUTE MARKETING, INC.
Category: otc | Type: HUMAN OTC DRUG LABEL
Date: 20200605

ACTIVE INGREDIENTS: ALCOHOL 70 mL/100 mL
INACTIVE INGREDIENTS: TRIETHANOLAMINE DODECYLBENZENESULFONATE 0.1 mL/100 mL; GLYCERIN 1 mL/100 mL; CARBOMER COPOLYMER TYPE A (ALLYL PENTAERYTHRITOL CROSSLINKED) 0.25 mL/100 mL; WATER 28.65 mL/100 mL

Active Ingredient(s)

Ethyl Alcohol 70% v/v. Purpose: Antiseptic

Purpose

Antiseptic

Use

Hand Sanitizer to reduce bacterial organisms on the skin.

Warnings

For external use only. Flammable. Keep away from heat or flame

WHEN USING

Avoid contact with eyes. If contact occurs, flush eyes throughly with water.

Stop use and ask a doctor if irritation or rash develops and persists. T
Keep out of reach of children. If swallowed, get medical help or contact a Poison Control Center immediately.

Stop use and ask a doctor if irritation or rash develops and persists.

Keep out of reach of children. If swallowed, get medical help or contact a Poison Control Center right away.

Directions

- Dispense a small amount onto palm of hand and rub briskly and thoroughly over surfaces of both hands until dry.
- Children under 6 years of age should be supervised while using this product.

Other information

- Store below 110 °F (43 °C)
- May discolor certain fabrics or surfaces.

Inactive ingredients

Water, Glycerin, Acrylates/c10-30 Alkyl Acrylate Crosspolymer, Triethanolamine